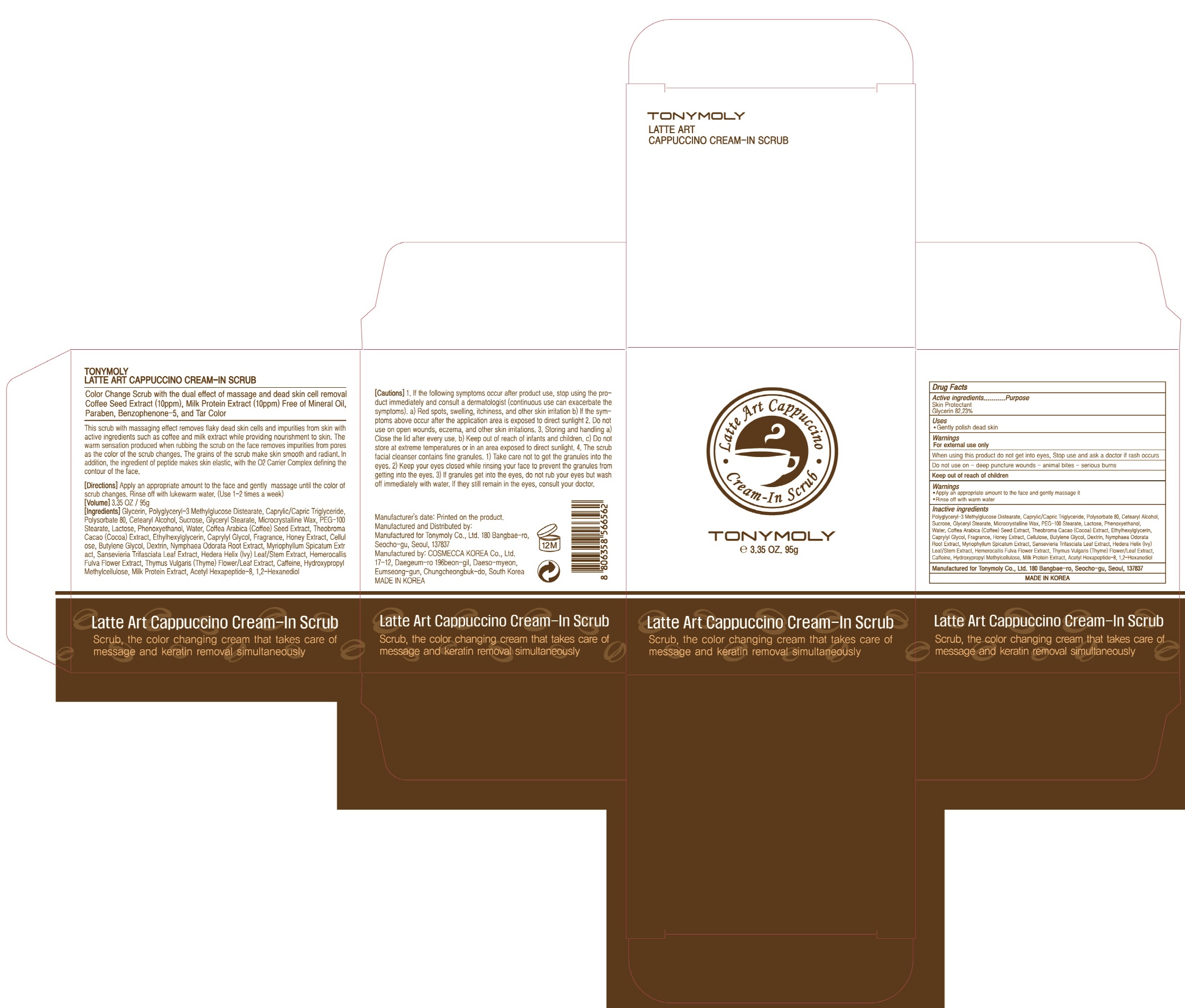 DRUG LABEL: Tonymoly Latte Art Cappuccino Cre am In Scrub
NDC: 59078-322 | Form: CREAM
Manufacturer: TONYMOLY CO.,LTD
Category: otc | Type: HUMAN OTC DRUG LABEL
Date: 20161128

ACTIVE INGREDIENTS: Glycerin 78.1 g/95 g
INACTIVE INGREDIENTS: Polysorbate 80; Sucrose

ACTIVE INGREDIENT

Active Ingredient: Glycerin 82.23%

INACTIVE INGREDIENT

Inactive Ingredients: Polyglyceryl-3 Methylglucose Distearate, Caprylic/Capric Triglyceride, Polysorbate 80, Cetearyl Alcohol, Sucrose, Glyceryl Stearate, Microcrystalline Wax, PEG-100 Stearate, Lactose, Phenoxyethanol, Water, Coffea Arabica (Coffee) Seed Extract, Theobroma Cacao (Cocoa) Extract, Ethylhexylglycerin, Caprylyl Glycol, Fragrance, Honey Extract, Cellulose, Butylene Glycol, Dextrin, Nymphaea Odorata Root Extract, Myriophyllum Spicatum Extract, Sansevieria Trifasciata Leaf Extract, Hedera Helix (Ivy) Leaf/Stem Extract, Hemerocallis Fulva Flower Extract, Thymus Vulgaris (Thyme) Flower/Leaf Extract, Caffeine, Hydroxypropyl Methylcellulose, Milk Protein Extract, Acetyl Hexapeptide-8, 1,2-Hexanediol

PURPOSE

Purpose: Skin Protectant

WARNINGS

Warnings: For external use only When using this product do not get into eyes, Stop use and ask a doctor if rash occurs Do not use on - deep puncture wounds - animal bites - serious burns Keep out of reach of children

KEEP OUT OF REACH OF CHILDREN

Uses

Uses: Gently polish dead skin

Directions

Directions: - Apply an appropriate amount to the face and gently massage it - Rinse off with warm water